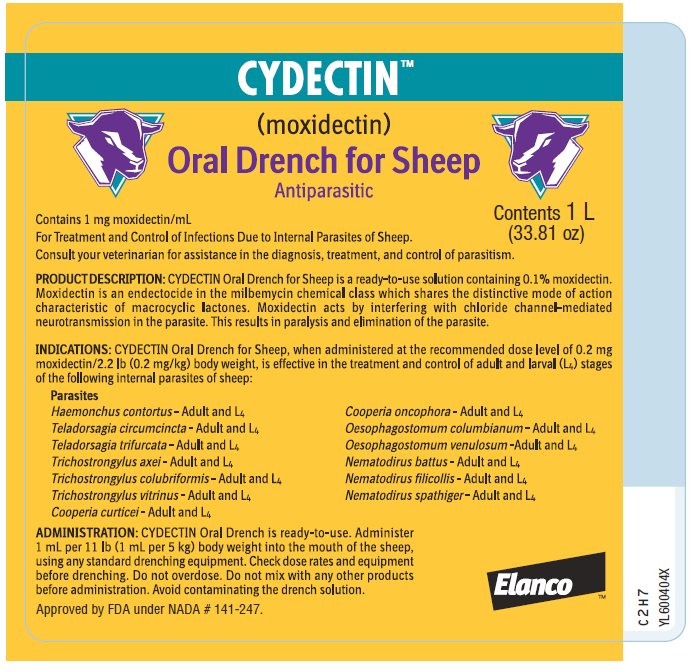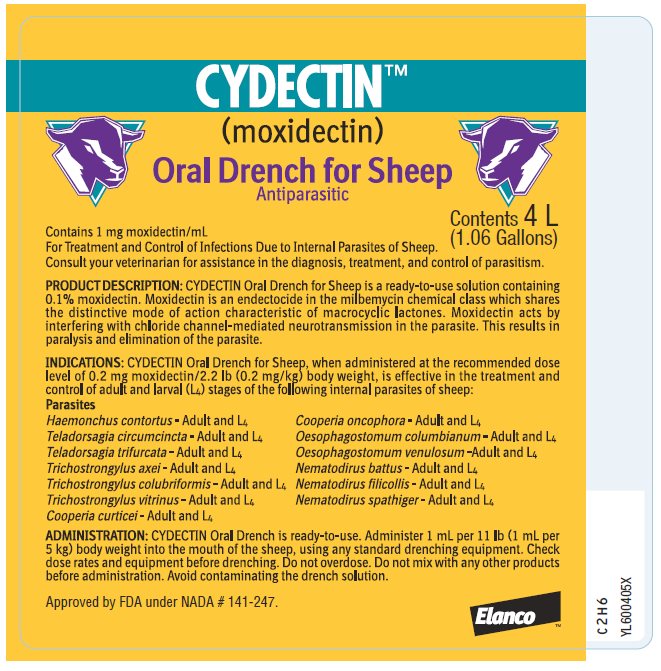 DRUG LABEL: Cydectin
NDC: 58198-0029 | Form: LIQUID
Manufacturer: Elanco US Inc.
Category: animal | Type: OTC ANIMAL DRUG LABEL
Date: 20250124

ACTIVE INGREDIENTS: moxidectin 1 mg/1 mL

CYDECTINTM
(moxidectin)
Oral Drench for Sheep
Antiparasitic

Approved by FDA under NADA # 141-247

Contains 1 mg moxidectin/mL

For Treatment and Control of Infections Due to Internal Parasites of Sheep.

Consult your veterinarian for assistance in the diagnosis, treatment, and control of parasitism.

PRODUCT DESCRIPTION:

CYDECTIN Oral Drench for Sheep is a ready-to-use solution containing 0.1% moxidectin. Moxidectin is an endectocide in the milbemycin chemical class which shares the distinctive mode of action characteristic of macrocyclic lactones. Moxidectin acts by interfering with chloride channel-mediated neurotransmission in the parasite. This results in paralysis and elimination of the parasite.

INDICATIONS:

CYDECTIN Oral Drench for Sheep, when administered at the recommended dose level of 0.2 mg moxidectin/2.2 lb (0.2 mg/kg) body weight, is effective in the treatment and control of adult and larval (L4) stages of the following internal parasites of sheep:

Parasites

Haemonchus contortus - Adult and L4 Cooperia oncophora - Adult and L4
Teladorsagia circumcincta - Adult and L4 Oesophagostomum columbianum - Adult and L4
Teladorsagia trifurcata - Adult and L4 Oesophagostomum venulosum - Adult and L4
Trichostrongylus axei - Adult and L4 Nematodirus battus - Adult and L4
Trichostrongylus colubriformis - Adult and L4 Nematodirus filicollis - Adult and L4
Trichostrongylus vitrinus - Adult and L4 Nematodirus spathiger - Adult and L4
Cooperia curticei - Adult and L4

ADMINISTRATION:

CYDECTIN Oral Drench is ready-to-use. Administer 1 mL per 11 lb (1 mL per 5 kg) body weight into the mouth of the sheep, using any standard drenching equipment. Check dose rates and equipment before drenching. Do not overdose. Do not mix with any other products before administration. Avoid contaminating the drench solution.

DOSAGE:

The recommended rate of administration for CYDECTIN Oral Drench for Sheep is 1 mL per 11 lb (5kg) body weight to provide 0.2 mg moxidectin/2.2 lb (0.2 mg/kg) body weight. The table below will assist in the calculation of the appropriate volume of drench in 1.0 mL increments and it must be administered based on the weight of animal being treated.

Body Weight |  | Dose | Body Weight |  | Dose | Body Weight |  | Dose
11 lb | 5 kg | 1 mL | 66 lb | 30 kg | 6 mL | 121 lb | 55 kg | 11 mL
22 lb | 10 kg | 2 mL | 77 lb | 35 kg | 7 mL | 132 lb | 60 kg | 12 mL
33 lb | 15 kg | 3 mL | 88 lb | 40 kg | 8 mL | 143 lb | 65 kg | 13 mL
44 lb | 20 kg | 4 mL | 99 lb | 45 kg | 9 mL | 154 lb | 70 kg | 14 mL
55 lb | 25 kg | 5 mL | 110 lb | 50 kg | 10 mL | 165 lb | 75 kg | 15 mL

Do not underdose. Ensure each animal receives a complete dose based on a current body weight. Underdosing may result in ineffective treatment, and encourage the development of parasite resistance.

HUMAN WARNINGS:

Not for use in humans. Keep this and all drugs out of the reach of children.

For product questions, to report adverse reactions, or for a copy of the Safety Data Sheet (SDS), call Elanco Product & Veterinary Support at 1-800-428-4441.

To obtain a copy of the safety data sheet (SDS) which provides more detailed occupational safety information or to report adverse reactions attributable to exposure to this product, call 1-800-428-4441.

RESIDUE WARNINGS:

Sheep must not be slaughtered for human consumption within 7 days of treatment. Because a withholding time in milk has not been established for this product, do not use in female sheep providing milk for human consumption.

ENVIRONMENTAL WARNINGS:

Studies indicate that when moxidectin comes in contact with the soil, it readily and tightly binds to the soil and becomes inactive. Free moxidectin may adversely affect fish and certain aquatic organisms. Do not contaminate water by direct application or by improper disposal of drug containers.

ANIMAL SAFETY WARNINGS:

CYDECTIN Oral Drench for Sheep has been formulated specifically for oral use in sheep and should not be given by any other route of administration. Do not use in sick, debilitated, or underweight animals. This product should not be used in other animal species as severe adverse reactions, including fatalities in dogs, may result.

OTHER WARNINGS:

- Parasite resistance may develop to any dewormer, and has been reported for most classes of dewormers.
- Treatment with a dewormer used in conjunction with parasite management practices appropriate to the geographic area and the animal(s) to be treated may slow the development of parasite resistance.
- Fecal examinations or other diagnostic tests and parasite management history should be used to determine if the product is appropriate for the herd/flock, prior to the use of any dewormer. Following the use of any dewormer, effectiveness of treatment should be monitored (for example, with the use of a fecal egg count reduction test or another appropriate method).
- A decrease in a drug's effectiveness over time as calculated by fecal egg count reduction tests may indicate the development of resistance to the dewormer administered. Your parasite management plan should be adjusted accordingly based on regular monitoring.
- Macrocyclic lactones provide prolonged drug exposure that may increase selection pressure for resistant parasites. This effect may be more pronounced in extended-release formulations.

ANIMAL SAFETY:

A well-controlled U.S. study has demonstrated an adequate margin of safety to allow treatment of sheep four months of age and older with CYDECTIN Oral Drench. In this study no signs of toxicity were seen in sheep given up to 5 times the recommended dose. Reproductive safety studies evaluating the use of CYDECTIN Oral Drench in breeding ewes and rams have not been conducted in the U.S.

STORAGE:

Store product at or below 77˚F (25˚C). Protect from light.

DISPOSAL:

Do not contaminate water by direct application or by improper disposal of drug containers. Dispose of containers in an approved landfill or by incineration.

Manufactured for: CYDECTIN, Elanco and the diagonal bar logo
Elanco US Inc. are trademarks of Elanco or its affiliates.
Greenfield, IN 46140 U.S.A © 2022 Elanco or its affiliates.
Made in China Restricted Drug (CA) - Use Only As Directed
Made in Italy

ElancoTM

YL600404X

YL600405X

Principal Display Panel - Bottle Label

CYDECTINTM
(moxidectin)

Oral Drench for Sheep
Antiparasitic

Contents 1 L
(33.81 oz)

Contains 1 mg moxidectin/mL

For Treatment and Control of Infections Due to Internal Parasites of Sheep.
Consult your veterinarian for assistance in the diagnosis, treatment, and control of parasitism.

Approved by FDA under NADA # 141-247.

ElancoTM

CYDECTINTM
(moxidectin)

Oral Drench for Sheep
Antiparasitic

Contents 4 L
(1.06 Gallons)

Contains 1 mg moxidectin/mL

For Treatment and Control of Infections Due to Internal Parasites of Sheep.
Consult your veterinarian for assistance in the diagnosis, treatment, and control of parasitism.

Approved by FDA under NADA # 141-247.

ElancoTM